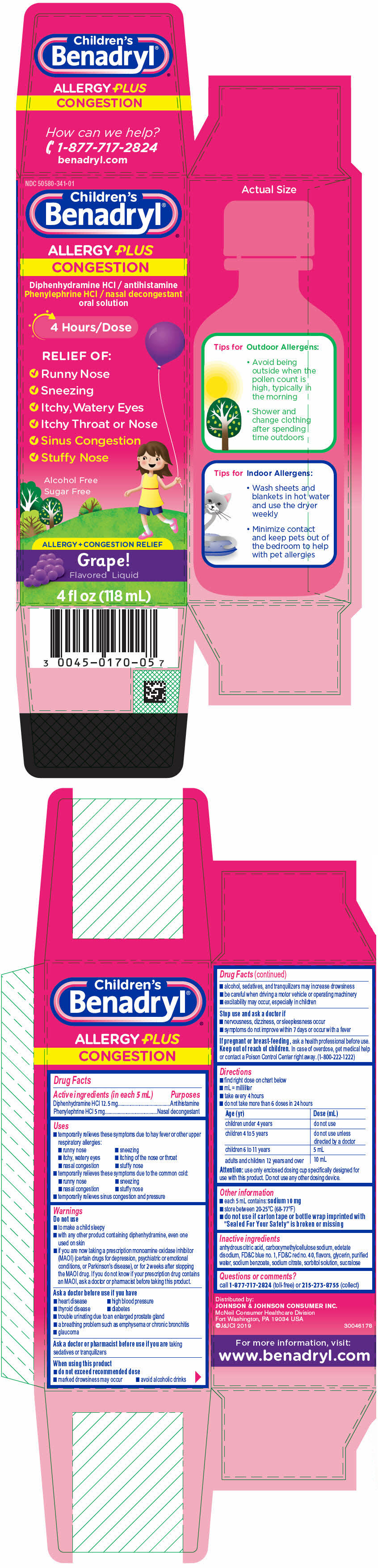 DRUG LABEL: Childrens Benadryl Allergy Plus Congestion
NDC: 50580-341 | Form: SOLUTION
Manufacturer: Kenvue Brands LLC
Category: otc | Type: HUMAN OTC DRUG LABEL
Date: 20241108

ACTIVE INGREDIENTS: DIPHENHYDRAMINE HYDROCHLORIDE 12.5 mg/5 mL; PHENYLEPHRINE HYDROCHLORIDE 5 mg/5 mL
INACTIVE INGREDIENTS: ANHYDROUS CITRIC ACID; CARBOXYMETHYLCELLULOSE SODIUM, UNSPECIFIED; EDETATE DISODIUM; FD&C BLUE NO. 1; FD&C RED NO. 40; GLYCERIN; WATER; SODIUM BENZOATE; SODIUM CITRATE, UNSPECIFIED FORM; SORBITOL SOLUTION; SUCRALOSE

Childrens Benadryl Allergy Plus Congestion

Drug Facts

ACTIVE INGREDIENT

PURPOSE

Active ingredients (in each 5 mL) | Purposes
Diphenhydramine HCl 12.5 mg | Antihistamine
Phenylephrine HCl 5 mg | Nasal decongestant

Uses

- temporarily relieves these symptoms due to hay fever or other upper respiratory allergies:
  - runny nose
  - sneezing
  - itchy, watery eyes
  - itching of the nose or throat
  - nasal congestion
  - stuffy nose
- temporarily relieves these symptoms due to the common cold:
  - runny nose
  - sneezing
  - nasal congestion
  - stuffy nose
- temporarily relieves sinus congestion and pressure

Warnings

Do not use

- to make a child sleepy
- with any other product containing diphenhydramine, even one used on skin
- if you are now taking a prescription monoamine oxidase inhibitor (MAOI) (certain drugs for depression, psychiatric or emotional conditions, or Parkinson's disease), or for 2 weeks after stopping the MAOI drug. If you do not know if your prescription drug contains an MAOI, ask a doctor or pharmacist before taking this product.

Ask a doctor before use if you have

- heart disease
- high blood pressure
- thyroid disease
- diabetes
- trouble urinating due to an enlarged prostate gland
- a breathing problem such as emphysema or chronic bronchitis
- glaucoma

Ask a doctor or pharmacist before use if you are taking sedatives or tranquilizers

When using this product

- do not exceed recommended dose
- marked drowsiness may occur
- avoid alcoholic drinks
- alcohol, sedatives, and tranquilizers may increase drowsiness
- be careful when driving a motor vehicle or operating machinery
- excitability may occur, especially in children

Stop use and ask a doctor if

- nervousness, dizziness, or sleeplessness occur
- symptoms do not improve within 7 days or occur with a fever

PREGNANCY OR BREAST FEEDING

If pregnant or breast-feeding, ask a health professional before use.

Keep out of reach of children. In case of overdose, get medical help or contact a Poison Control Center right away. (1-800-222-1222)

Directions

- find right dose on chart below
- mL = milliliter
- take every 4 hours
- do not take more than 6 doses in 24 hours

Age (yr) | Dose (mL)
children under 4 years | do not use
children 4 to 5 years | do not use unless directed by a doctor
children 6 to 11 years | 5 mL
adults and children 12 years and over | 10 mL

Attention: use only enclosed dosing cup specifically designed for use with this product. Do not use any other dosing device.

Other information

- each 5 mL contains: sodium 10 mg
- store between 20-25°C (68-77°F)
- do not use if carton tape or bottle wrap imprinted with "Sealed For Your Safety" is broken or missing

Inactive ingredients

anhydrous citric acid, carboxymethylcellulose sodium, edetate disodium, FD&C blue no. 1, FD&C red no. 40, flavors, glycerin, purified water, sodium benzoate, sodium citrate, sorbitol solution, sucralose

Questions or comments?

call 1-877-717-2824 (toll-free) or 215-273-8755 (collect)

PRINCIPAL DISPLAY PANEL

NDC 50580-341-01

Children's
Benadryl®

ALLERGY PLUS
CONGESTION

Diphenhydramine HCl / antihistamine
Phenylephrine HCl / nasal decongestant
oral solution

4 Hours/Dose

RELIEF OF:

- Runny Nose
- Sneezing
- Itchy, Watery Eyes
- Itchy Throat or Nose
- Sinus Congestion
- Stuffy Nose

Alcohol Free
Sugar Free

ALLERGY + CONGESTION RELIEF

Grape!
Flavored Liquid

4 fl oz (118 mL)